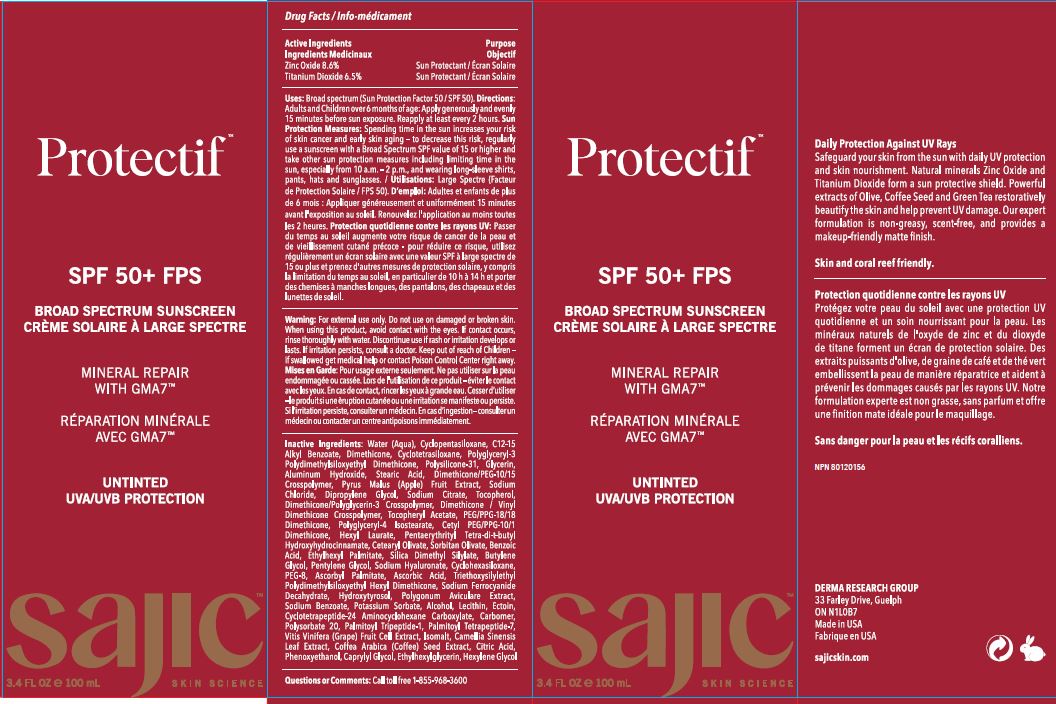 DRUG LABEL: Protectif Untinted
NDC: 82038-007 | Form: CREAM
Manufacturer: Derma Research Group Inc.
Category: otc | Type: HUMAN OTC DRUG LABEL
Date: 20240613

ACTIVE INGREDIENTS: TITANIUM DIOXIDE 6.5 g/100 g; ZINC OXIDE 8.6 g/100 g
INACTIVE INGREDIENTS: TOCOPHEROL; PEG/PPG-18/18 DIMETHICONE; POLYGLYCERYL-4 ISOSTEARATE; HEXYLENE GLYCOL; DIMETHICONE; CETYL PEG/PPG-10/1 DIMETHICONE (HLB 4); HYDROXYTYROSOL; DIMETHICONE/VINYL DIMETHICONE CROSSPOLYMER (SOFT PARTICLE); PALMITOYL TETRAPEPTIDE-7; ASCORBIC ACID; LECITHIN, SOYBEAN; ARABICA COFFEE BEAN; SODIUM FERROCYANIDE DECAHYDRATE; POLYGONUM AVICULARE TOP; SODIUM BENZOATE; ALCOHOL; CARBOMER HOMOPOLYMER, UNSPECIFIED TYPE; CYCLOMETHICONE 4; GLYCERIN; STEARIC ACID; DIPROPYLENE GLYCOL; CYCLOTETRAPEPTIDE-24 AMINOCYCLOHEXANE CARBOXYLATE; POLYSORBATE 20; CAPRYLYL GLYCOL; HYALURONATE SODIUM; HEXYL LAURATE; ALUMINUM HYDROXIDE; PALMITOYL TRIPEPTIDE-1; WINE GRAPE; CETEARYL OLIVATE; ALKYL (C12-15) BENZOATE; POLYGLYCERYL-3 POLYDIMETHYLSILOXYETHYL DIMETHICONE (4000 MPA.S); DIMETHICONE/PEG-10/15 CROSSPOLYMER; APPLE; POLYSILICONE-15; POLYETHYLENE GLYCOL 400; BUTYLENE GLYCOL; CYCLOMETHICONE 5; PENTAERYTHRITOL TETRAKIS(3-(3,5-DI-TERT-BUTYL-4-HYDROXYPHENYL)PROPIONATE); SORBITAN OLIVATE; ASCORBYL PALMITATE; PHENOXYETHANOL; ETHYLHEXYLGLYCERIN; SODIUM CITRATE; DIMETHICONE/POLYGLYCERIN-3 CROSSPOLYMER; GREEN TEA LEAF; WATER; SODIUM CHLORIDE; .ALPHA.-TOCOPHEROL ACETATE; BENZOIC ACID; SILICA DIMETHYL SILYLATE; PENTYLENE GLYCOL; CITRIC ACID MONOHYDRATE; ETHYLHEXYL PALMITATE; CYCLOMETHICONE 6; TRIETHOXYSILYLETHYL POLYDIMETHYLSILOXYETHYL HEXYL DIMETHICONE; POTASSIUM SORBATE; ECTOINE; ISOMALT

Drug Facts

ACTIVE INGREDIENT

Active Ingredients: Zinc Oxide 8.6%, Titanium Dioxide 6.5%

Purpose: Sun Protectant

INDICATIONS AND USAGE

Uses: Broad spectrum (Sun Protection Factor 50 /SPF 50).

WARNINGS

Warning: For external use only.

Do not use on damaged or broken skin.

When using this product avoid contact with the eyes. If contact occurs, rinse thoroughly with water.

STOP USE

Discontinue use if rash or irritation develops or lasts. If irritation persists, consult a doctor.

Keep out of reach of Children -if swallowed get medical help or contact Poison Control Center right away.

DOSAGE AND ADMINISTRATION

Directions: Adults and Children over 6 months of age: Apply generously and evenly 15 minutes before sun exposure. Reapply at least every 2 hours. Sun Protection Measures: Spending time in the sun increases your risk of skin cancer and early skin aging - to decrease this risk, regularly use a sunscreen with a Broad Spectrum SPF value of 15 or higher and take other sun protection measures including limiting time in the sun, especially from 10 a.m. - 2 p.m., and wearing long-sleeve shirts, pants, hats and sunglasses

OTHER SAFETY INFORMATION

Sun Protection Measures: Spending time in the sun increases your risk of skin cancer and early skin aging - to decrease this risk, regularly use a sunscreen with a Broad Spectrum SPF value of 15 or higher and take other sun protection measures including limiting time in the sun, especially from 10 a.m. - 2 p.m., and wearing long-sleeve shirts, pants, hats and sunglasses

INACTIVE INGREDIENT

Inactive ingredients: Water (Aqua), Cyclopentasiloxane, C12-15 Alkyl Benzoate, Dimethicone, Cyclotetrasiloxane, Polyglyceryl-3 Polydimethylsiloxyethyl Dimethicone, Polysilicone-31, Glycerin, Aluminum Hydroxide, Stearic Acid, Dimethicone/PEG-10/15 Crosspolymer, Pyrus Malus (Apple) Fruit Extract, Sodium Chloride, Dipropylene Glycol, Sodium Citrate, Tocopherol, Dimethicone/Polyglycerin-3 Crosspolymer, Dimethicone / Vinyl Dimethicone Crosspolymer, Tocopheryl Acetate, PEG/PPG-18/18 Dimethicone, Polyglyceryl-4 Isostearate, Cetyl PEG/PPG-1011 Dimethicone, Hexyl Laurate, Pentaerythrityl Tetra-di-t-butyl Hydroxyhydrocinnamate, Cetearyl Olivate, Sorbitan Olivate, Benzoic Acid, Ethylhexyl Palmitate, Silica Dimethyl Silylate, Butylene Glycol, Pentylene Glycol, Sodium Hyaluronate, Cyclohexasiloxane, PEG-8, Ascorbyl Palmitate, Ascorbic Acid, Triethoxysilylethyl Polydimethylsiloxyethyl Hexyl Dimethicone, Sodium Ferrocyanide Deca hydrate, Hydroxytyrosol, Polygonum Aviculare Extract, Sodium Benzoate, Potassium Sorbate, Alcohol, Lecithin, Ectoin, Cyclotetra peptide-24 Aminocyclohexane Carboxylate, Carbomer, Polysorbate 20, Palmitoyl Tripeptide-1, Palmitoyl Tetra peptide-7, Vitis Vinifera (Grape) Fruit Cell Extract, Isomalt, Camellia Sinensis Leaf Extract, Coffee Arabica (Coffee) Seed Extract, Citric Acid, Phenoxyethanol, Caprylyl Glycol, Ethylhexylglycerin, Hexylene Glycol